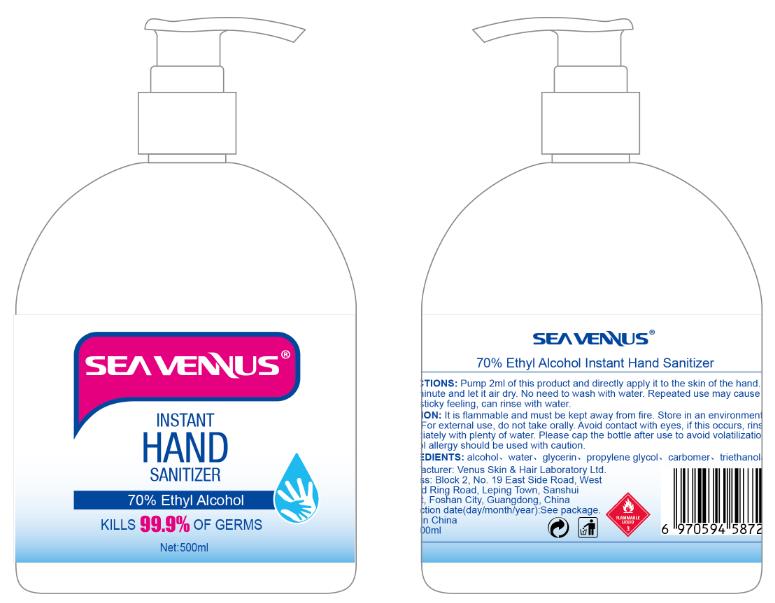 DRUG LABEL: Instant Hand Sanitizer
NDC: 54708-015 | Form: LIQUID
Manufacturer: Venus Skin & Hair Laboratory Ltd.
Category: otc | Type: HUMAN OTC DRUG LABEL
Date: 20200520

ACTIVE INGREDIENTS: ALCOHOL 350 mL/500 mL
INACTIVE INGREDIENTS: GLYCERIN; CARBOMER INTERPOLYMER TYPE A (ALLYL SUCROSE CROSSLINKED); WATER; PROPYLENE GLYCOL; TROLAMINE

Venus, Hand Sanitizer, 70% Ethyl Alcohol, Liquid, 500mL, Bottle-Pump

Active Ingredient(s)

Ethyl Alcohol 70% v/v. Purpose: Antimicrobial

Purpose

Antimicrobial.

Use

Uses for handwashing to decrease bacteria on the skin.

Warnings

It is flammable and must kept away from fire.
For external use, do not take orally.

Do not use

Avoid contact with eyes, if this occurs, rinse immediately with plenty of water.
Alcohol allergy should be used with caution.

When using this product, do not use in or near the eyes or wound.

Stop use and ask a doctor if irritation and redness develop and persist for more than 72 hours.

Keep out of reach of children. If swallowed, get medical help or contact a poison control center right away.

Directions

Take 2ml of this product and directly apply it to the skin of the hand.
Leave for 1 minute and let it air dry.
No need to wash with water.
Repeated use may cause a slight sticky feeling, can rinse with water.

Other information

Store in an environment below 50℃.
Please cap the bottle after use to avoid volatilization.

Inactive ingredients

Water, Glycerin, Propylene Glycol, Carbomer, Triethanolamine.